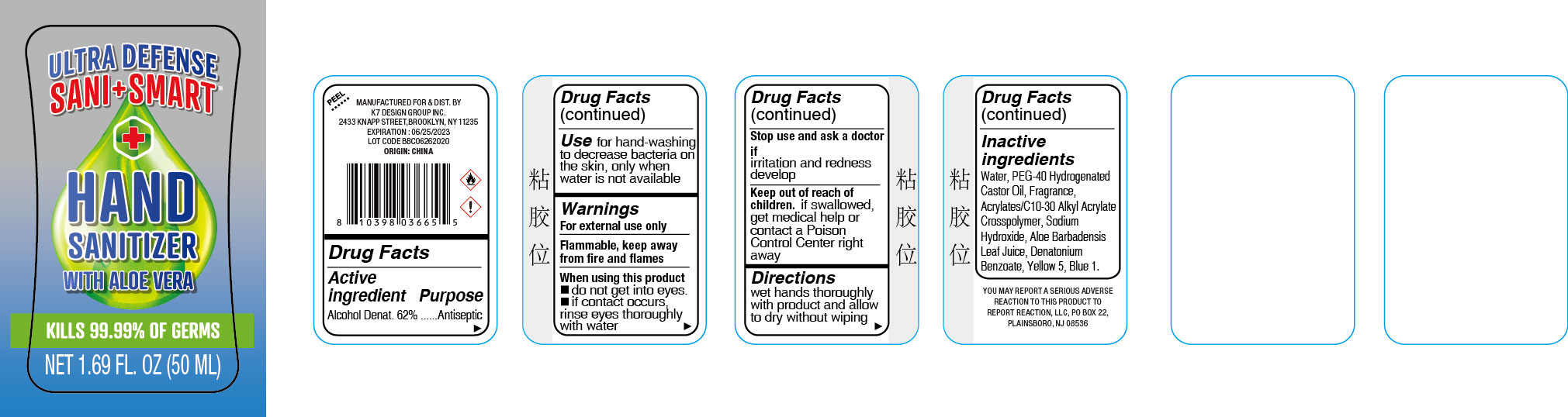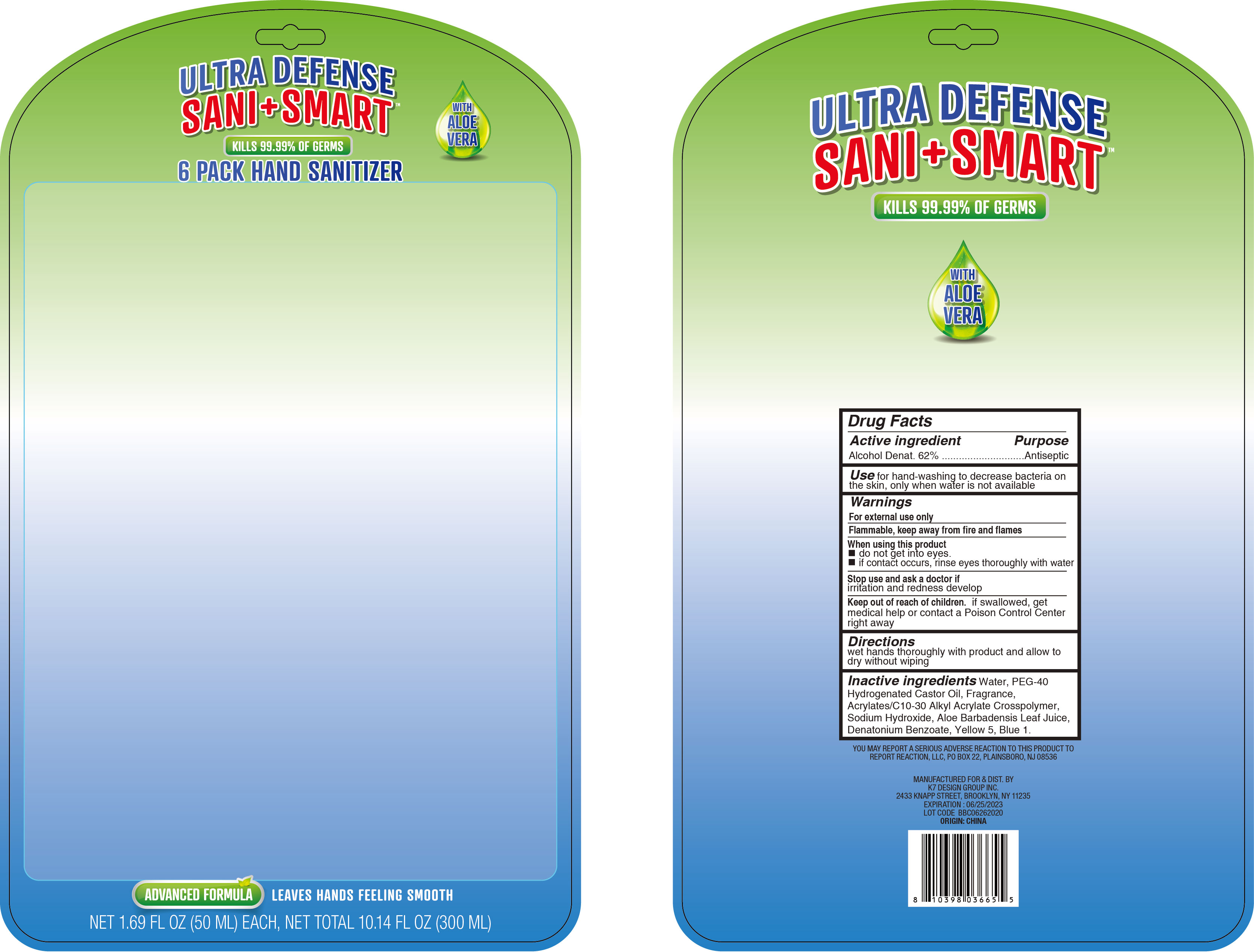 DRUG LABEL: Hand Sanitizer
NDC: 74177-028 | Form: LIQUID
Manufacturer: K7 Design Group Inc.
Category: otc | Type: HUMAN OTC DRUG LABEL
Date: 20200703

ACTIVE INGREDIENTS: ALCOHOL 62 mL/100 mL
INACTIVE INGREDIENTS: ALOE VERA LEAF; GLYCERIN; WATER; DENATONIUM BENZOATE; FD&C BLUE NO. 1; POLYOXYL 40 HYDROGENATED CASTOR OIL; SODIUM HYDROXIDE; FD&C YELLOW NO. 5

K7 BBC Aloe Hand Sanitizer 62 Blstr

Active Ingredient

Alcohol Denat. 62%

Purpose

Antiseptic

Use

for hand-washing to help decrease bacteria on the skin, only when water is not available

Warnings

For external use only. Flammable, keep away from fire and flames.

When using this product

■ do not get into eyes.

■ if contact occurs, rinse eyes throughly with water.

Stop use and ask a doctor if

irritation and redness develops and persists.

Keep out of reach of children

if swallowed, get medical help or contact a Poison Control Center right away.

Directions

wet hands thoroughly with product and allow to dry without wiping

Inactive ingredients

Water, PEG-40 Hydrogenated Castor Oil, Fragrance, Acrylates/C10-30 Alkyl Acrylates Crosspolymer, Sodium Hydroxide, Aloe Barbadensis Leaf Juice, Denatonium Benzoate, Yellow 5, Blue 1